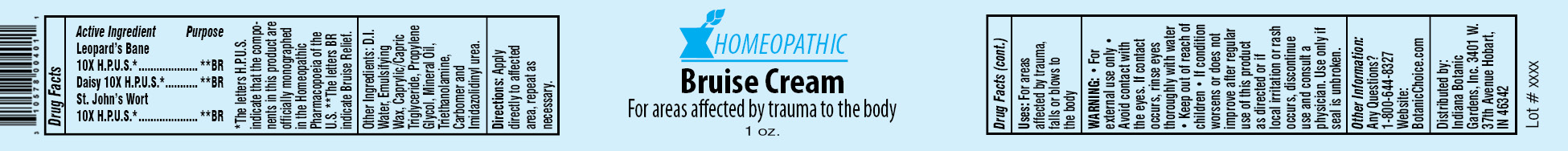 DRUG LABEL: Homeopathic Bruise
NDC: 10578-004 | Form: CREAM
Manufacturer: Indiana Botanic Gardens
Category: homeopathic | Type: HUMAN OTC DRUG LABEL
Date: 20120427

ACTIVE INGREDIENTS: ARNICA MONTANA 10 [hp_X]/28 g; BELLIS PERENNIS 10 [hp_X]/28 g; HYPERICUM PERFORATUM 10 [hp_X]/28 g
INACTIVE INGREDIENTS: WATER; CETOSTEARYL ALCOHOL; POLYSORBATE 60; TRICAPRYLIN; PROPYLENE GLYCOL; MINERAL OIL; TROLAMINE; CARBOMER 934; IMIDUREA

Homeopathic Bruise Cream

Active Ingredients

Leopard’s Bane 10X H.P.U.S.*

Daisy 10X H.P.U.S.*

St. John’s Wort 10X H.P.U.S.*

Purpose

**BR

**BR

**BR

*The letters H.P.U.S. indicate that the components in this product are officially monographed in the Homeopathic Pharmacopoeia of the U.S. **The letters BR indicate Bruise Relief.

Other Ingredients:

D.I. Water, Emulsifying Wax, Caprylic/Capric Triglyceride, Propylene Glycol, Mineral Oil, Triethanolamine, Carbomer and Imidazolidinyl urea.

Directions:

Apply directly to affected area, repeat as necessary.

Uses:

For areas affected by trauma, falls or blows to the body

WARNING:

- for external use only
- Avoid contact with the eyes. If contact occurs, rinse eyes thoroughly with water

- Keep out of reach of children

STOP USE

- If condition worsens or does not improve after regular use of this product as directed or if local irritation or rash occurs, discontinue use and consult a physician.

Use only if seal is unbroken.

Other Information:

Any Questions?

1-800-644-8327

Website:

BotanicChoice.com

Distributed by:

Indiana Botanic Gardens, Inc. 3401 W. 37th Avenue Hobart, IN 46342

Homeopathic Bruise Cream

For areas affected by trauma to the body

1 oz.